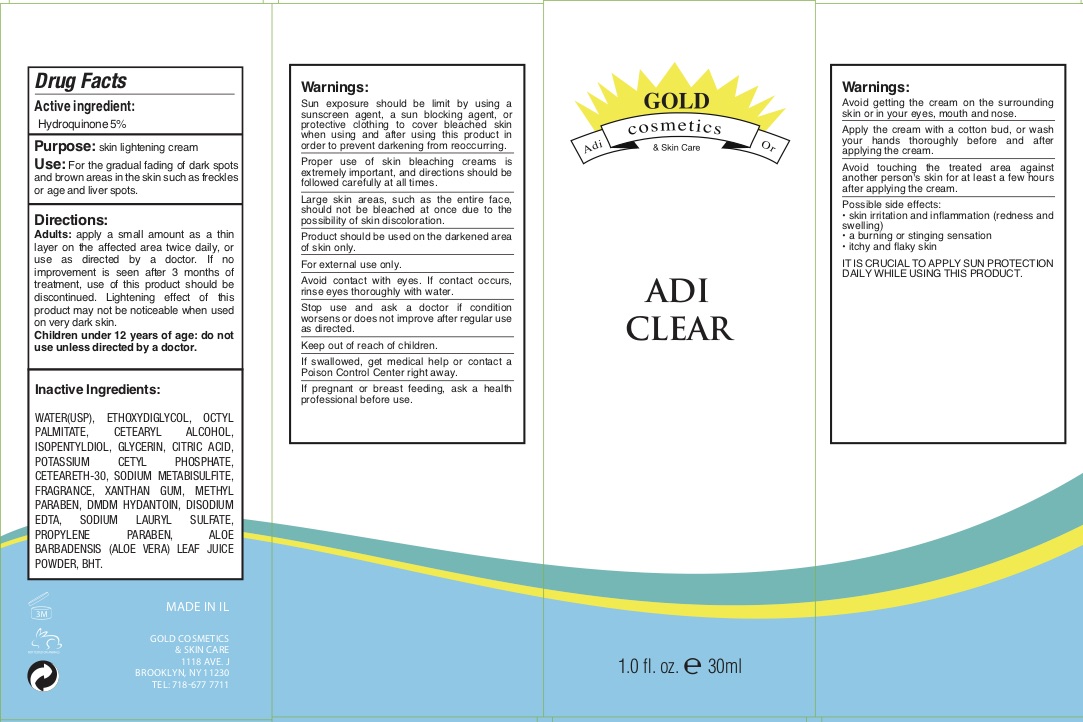 DRUG LABEL: Gold Cosmetics Adi Clear
NDC: 69435-1904 | Form: CREAM
Manufacturer: Peer Pharm Ltd
Category: otc | Type: HUMAN OTC DRUG LABEL
Date: 20190906

ACTIVE INGREDIENTS: HYDROQUINONE 5 mg/100 mL
INACTIVE INGREDIENTS: GLYCERIN; JOJOBA OIL; DECYL OLEATE; SODIUM DITHIONATE; XANTHAN GUM; PHENOXYETHANOL; CITRIC ACID MONOHYDRATE; POTASSIUM SORBATE; ALOE VERA LEAF; BUTYLATED HYDROXYTOLUENE; WATER; CETOSTEARYL ALCOHOL; STEARYL ALCOHOL; CETEARETH-30; STEARETH-21; STEARETH-2; EDETATE DISODIUM ANHYDROUS; CHLORPHENESIN; CETYL ALCOHOL; ALLANTOIN; ALPHA-TOCOPHEROL ACETATE

Adi CLear

ACTIVE INGREDIENT

Hydroquinone 5%

PURPOSE

Face cream for gradual fading of dark spots

INDICATIONS AND USAGE

Face cream for gradual fading of dark spots

Apply a very thin layer once a day, only at night, all over the face

DOSAGE AND ADMINISTRATION

Apply a very thin layer once a day, only at night, all over the face

Warnings:
Sun exposure should be limit by using a sunscreen agent, a sun blocking agent, or protective clothing to cover bleached skin
when using and after using this product in order to prevent darkening from reoccurring.
Proper use of skin bleaching creams is extremely important, and directions should be followed carefully at all times.
Large skin areas, such as the entire face, should not be bleached at once due to the possibility of skin discoloration.
Product should be used on the darkened area of skin only.
For external use only.
Avoid contact with eyes. If contact occurs, rinse eyes thoroughly with water.
Stop use and ask a doctor if condition worsens or does not improve after regular use as directed.
Keep out of reach of children.
If swallowed, get medical help or contact a Poison Control Center right away.
If pregnant or breast feeding, ask a health professional before use.

Keep out of reach of children